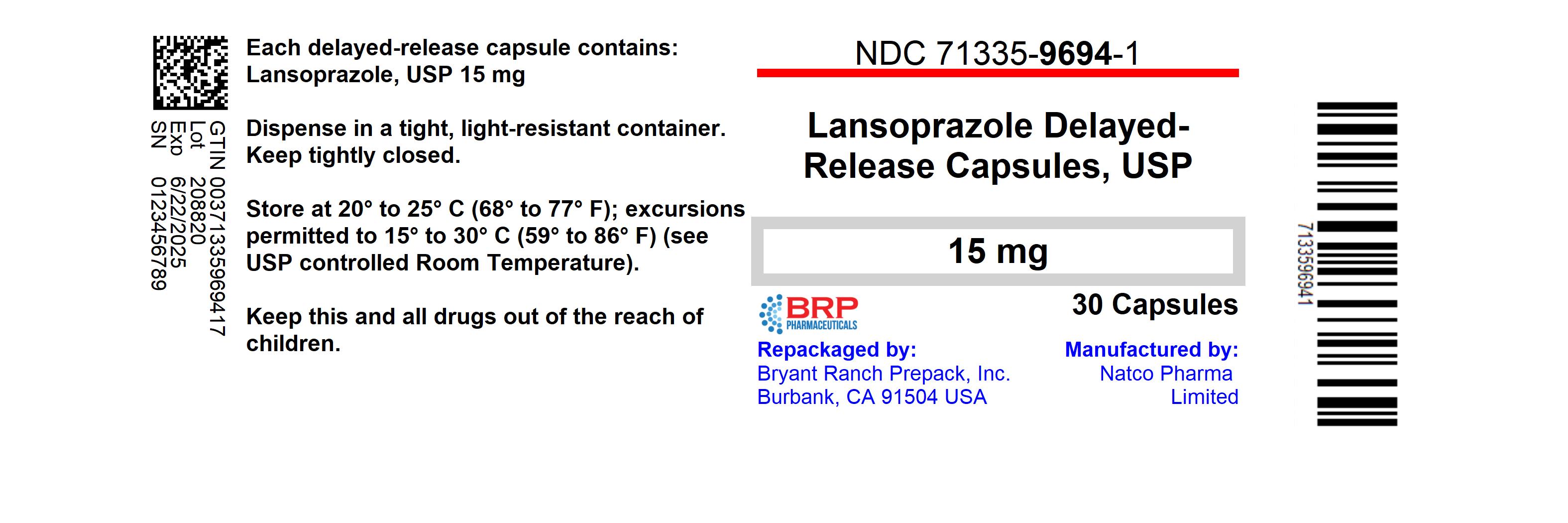 DRUG LABEL: Lansoprazole
NDC: 71335-9694 | Form: CAPSULE, DELAYED RELEASE
Manufacturer: Bryant Ranch Prepack
Category: otc | Type: HUMAN OTC DRUG LABEL
Date: 20230418

ACTIVE INGREDIENTS: LANSOPRAZOLE 15 mg/1 1
INACTIVE INGREDIENTS: ACETONE; D&C RED NO. 28; D&C YELLOW NO. 10; FD&C BLUE NO. 1; GELATIN, UNSPECIFIED; HYPROMELLOSE, UNSPECIFIED; ISOPROPYL ALCOHOL; MAGNESIUM CARBONATE; METHACRYLIC ACID - ETHYL ACRYLATE COPOLYMER (1:1) TYPE A; POLYSORBATE 80; SUCROSE; TALC; TITANIUM DIOXIDE; POLYETHYLENE GLYCOL, UNSPECIFIED; BUTYL ALCOHOL; ALCOHOL; POTASSIUM HYDROXIDE; PROPYLENE GLYCOL; WATER; SHELLAC; AMMONIA

Lansoprazole Delayed-Release Capsules USP, 15mg
Drug Facts

Active ingredient (in each capsule)

Lansoprazole 15 mg

Purpose

Acid reducer

Use

- treats frequent heartburn (occurs 2 or more days a week)
- not intended for immediate relief of heartburn; this drug may take 1 to 4 days for full effect

Warnings

Allergy alert: Do not use if you are allergic to lansoprazole

Do not use

- if you have trouble or pain swallowing food, vomiting with blood, or bloody or black stools. These may be signs of a serious condition. See your doctor.

Ask a doctor before use if you have

- liver disease
- had heartburn over 3 months. This may be a sign of a more serious condition.
- heartburn with lightheadedness, sweating or dizziness
- chest pain or shoulder pain with shortness of breath; sweating; pain spreading to arms, neck or shoulders; or lightheadedness
- frequent chest pain
- frequent wheezing, particularly with heartburn
- unexplained weight loss
- nausea or vomiting
- stomach pain

Ask a doctor or pharmacist before use if you are

taking a prescription drug. Acid reducers may interact with certain prescription drugs.

Stop use and ask a doctor if

- your heartburn continues or worsens
- you need to take this product for more than 14 days
- you need to take more than 1 course of treatment every 4 months
- you get diarrhea
- you develop a rash or joint pain

If pregnant or breast-feeding,

ask a health professional before use.

Keep out of reach of children.

In case of overdose, get medical help or contact a Poison Control Center right away (1-800-222-1222).

Directions

- adults 18 years of age and older
- this product is to be used once a day (every 24 hours), every day for 14 days
- it may take 1 to 4 days for full effect, although some people get complete relief of symptoms within 24 hours

14-Day Course of Treatment

- swallow 1 capsule with a glass of water before eating in the morning
- take every day for 14 days
- do not take more than 1 capsule a day
- swallow whole. Do not crush or chew capsules.
- do not use for more than 14 days unless directed by your doctor

Repeated 14-Day Courses (if needed)

- you may repeat a 14-day course every 4 months
- do not take for more than 14 days or more often than every 4 months unless directed by a doctor
- children under 18 years of age: ask a doctor before use. Heartburn in children may sometimes be caused by a serious condition.

Other information

- read the directions, warnings and package insert before use
- keep the package and package insert. They contain important information.
- store at 20-25°C (68-77°F)
- keep product out of high heat and humidity
- protect product from moisture
- close cap tightly after use

Inactive ingredients

acetone, D&C Red No. 28, D&C Yellow No. 10, FD&C Blue No. 1,gelatin, hypromellose, isopropyl alcohol, light magnesium carbonate, methacrylic acid copolymer type C, polyethylene glycol, polysorbate 80, sugar spheres (contain sucrose and starch), talc, titanium dioxide. Printing Ink contains butyl alcohol, dehydrated alcohol isopropyl alcohol, potassium hydroxide, propylene glycol, purified water, shellac, strong ammonia solution, titanium dioxide
Questions or comments? 1-844-874-7464

PATIENT INFORMATION

Treats Frequent Heartburn
Lansoprazole (lan-SO-pruh-zole)
Delayed-Release Capsules USP,
15 mg / Acid Reducer

- May take 1 to 4 days for full effect
- Sodium Free

Please read the entire package insert before taking Lansoprazole Delayed-Release Capsules, USP Save for future reference.
How Lansoprazole Delayed-Release Capsules, USP Treat Your Frequent Heartburn
Lansoprazole delayed-release capsules, USP stop acid production at the source - the pumps that release acid into the stomach. Lansoprazole delayed-release capsules, USP are taken once a day (every 24 hours), every day for 14 days.
What You Can Expect When Taking Lansoprazole Delayed-Release Capsules, USP
Frequent heartburn can occur anytime during the 24-hour period (day or night). Take lansoprazole delayed-release capsules, USP in the morning before eating. Lansoprazole delayed-release capsules, USP are clinically proven to treat frequent heartburn. Although some people get complete relief of symptoms within 24 hours, it may take 1 to 4 days for full effect. Make sure you take lansoprazole delayed-release capsules, USP every day for 14 days to treat your frequent heartburn.
Who Should Take Lansoprazole Delayed-Release Capsules, USP
Adults (18 years and older) with frequent heartburn - when you have heartburn 2 or more days a week.
Who Should NOT Take Lansoprazole Delayed-Release Capsules, USP
People who have one episode of heartburn a week or less, or who want immediate relief of heartburn.

How to Take Lansoprazole Delayed-Release Capsules, USP
14-DAY Course of Treatment

- Swallow 1 capsule with a glass of water before eating in the morning.
- Take every day for 14 days.
- Do not take more than 1 capsule a day.
- Swallow whole. Do not crush or chew capsules.
- Do not use for more than 14 days unless directed by your doctor.

When to Take Lansoprazole Delayed-Release Capsules, USP Again You may repeat a 14-day course of therapy every 4 months.
When to Talk to Your Doctor
Do not take for more than 14 days or more often than every 4 months unless directed by a doctor.

Warnings and When to Ask Your Doctor
Allergy alert: Do not use if you are allergic to lansoprazole
Do not use

- if you have trouble or pain swallowing food, vomiting with blood, or bloody or black stools. These may be signs of a serious condition. See your doctor.

Ask a doctor before use if you have

- liver disease
- had heartburn over 3 months. This may be a sign of a more serious condition.
- heartburn with lightheadedness, sweating or dizziness
- chest pain or shoulder pain with shortness of breath; sweating; pain spreading to arms, neck or shoulders; or lightheadedness
- frequent chest pain
- frequent wheezing, particularly with heartburn
- unexplained weight loss
- nausea or vomiting
- stomach pain

Ask a doctor or pharmacist before use if you are

- taking a prescription drug. Acid reducers may interact with certain prescription drugs.

Stop use ask a doctor if

- your heartburn continues or worsens
- you need to take this product for more than 14 days
- you need to take more than 1 course of treatment every 4 months
- you get diarrhea
- you develop a rash or joint pain

If pregnant or breast-feeding, ask a health professional before use.
Keep out of reach of children. In case of overdose, get medical
help or contact a Poison Control Center right away at 1-800-222-1222.

Tips for Managing Heartburn

- Avoid foods or drinks that are more likely to cause heartburn, such as rich, spicy, fatty and fried foods, chocolate, caffeine, alcohol and even some acidic fruits and vegetables.
- Eat slowly and do not eat big meals.
- Do not eat late at night or just before bedtime.
- Do not lie flat or bend over soon after eating.
- Raise the head of your bed.
- Wear loose-fitting clothing around your stomach.
- If you are overweight, lose weight.
- If you smoke, quit smoking.

Clinical studies prove Lansoprazole Delayed-Release Capsules, USP effectively treats frequent heartburn
In three clinical studies, lansoprazole delayed-release capsules, USP were shown to be significantly better than placebo in treating frequent heartburn.

How Lansoprazole Delayed-Release Capsules, USP are Sold
Lansoprazole delayed-release capsules, USP are available in 14 capsules, 28 capsules and 42 capsule sizes. These sizes contain one, two and three 14-day courses of treatment, respectively. Do not use for more than 14 days in a row unless directed by your doctor. For the 28 count (two 14-day courses) and the 42 count (three 14-day courses), you may repeat a 14-day course every 4 months.

For Questions or Comments About Lansoprazole Delayed-Release Capsules, USP
Call 1-844-474-7464
Manufactured by:
Natco Pharma Limited
Kothur - 509 228, India
Distributed by:
Rising Pharma Holdings, Inc.
East Brunswick, NJ 08816
Revised: 11/2020

HOW SUPPLIED

NDC: 71335-9694-1: 30 Capsules in a BOTTLE

NDC: 71335-9694-2: 15 Capsules in a BOTTLE

NDC: 71335-9694-3: 60 Capsules in a BOTTLE

NDC: 71335-9694-4: 90 Capsules in a BOTTLE

NDC: 71335-9694-5: 28 Capsules in a BOTTLE

PACKAGE LABEL

Lansoprazole DR 15mg Capsule (OTC)